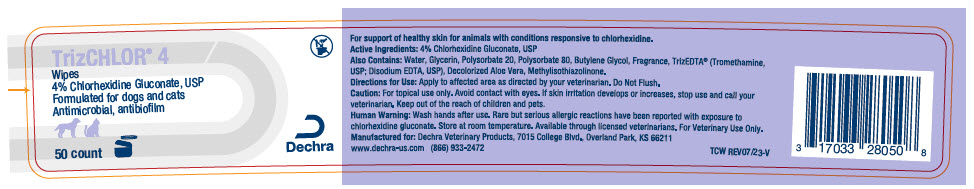 DRUG LABEL: TrizCHLOR 4 Wipes
NDC: 17033-279 | Form: CLOTH
Manufacturer: Dechra Veterinary Products
Category: animal | Type: OTC ANIMAL DRUG LABEL
Date: 20240308

ACTIVE INGREDIENTS: Chlorhexidine Gluconate 40 mg/1 1

TrizCHLOR® 4 Wipes

VETERINARY INDICATIONS

For support of healthy skin for animals with conditions responsive to chlorhexidine.

Active Ingredients: 4% Chlorhexidine Gluconate, USP

Also Contains: Water, Glycerine, Polysorbate 20, Polysorbate 80, Butylene Glycol, Fragrance, TrizEDTA® (Tromethamine, USP; Disodium EDTA, USP), Decolorized Aloe Vera, Methylisothiazolinone.

DOSAGE AND ADMINISTRATION

Directions for Use: Apply to affected area as directed by your veterinarian. Do Not Flush.

SAFE HANDLING WARNING

Caution: For topical use only. Avoid contact with eyes. If skin irritation develops or increases, stop use and call your veterinarian. Keep out of the reach of children and pets.

WARNINGS

Human Warning: Wash hands after use. Rare but serious allergic reactions have been reported with exposure to chlorhexidine gluconate. Store at room temperature. Available through licensed veterinarians. For Veterinary Use Only.

Manufactured for: Dechra Veterinary Products, 7015 College Blvd., Overland Park, KS 66211
www.dechra-us.com (866) 933-2472

TCW REV07/23-V

PRINCIPAL DISPLAY PANEL - 50 Wipe Container Label

TrizCHLOR® 4
Wipes
4% Chlorhexidine Gluconate, USP
Formulated for dogs and cats
Antimicrobial, antibiofilm

50 count

Dechra